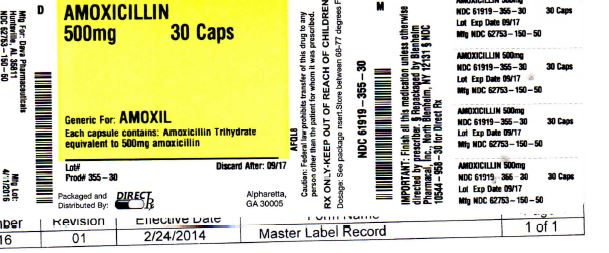 DRUG LABEL: AMOXICILLIN
NDC: 61919-355 | Form: CAPSULE
Manufacturer: DIRECTRX
Category: prescription | Type: HUMAN PRESCRIPTION DRUG LABEL
Date: 20160413

ACTIVE INGREDIENTS: AMOXICILLIN 500 mg/1 1
INACTIVE INGREDIENTS: ISOPROPYL ALCOHOL; BUTYL ALCOHOL; PROPYLENE GLYCOL; MAGNESIUM STEARATE; POTASSIUM HYDROXIDE; WATER; CELLULOSE, MICROCRYSTALLINE; SHELLAC; AMMONIA; FERROSOFERRIC OXIDE; ALCOHOL; FERRIC OXIDE YELLOW; TITANIUM DIOXIDE; GELATIN

AMOXICILLIN 500mg 30 TABS